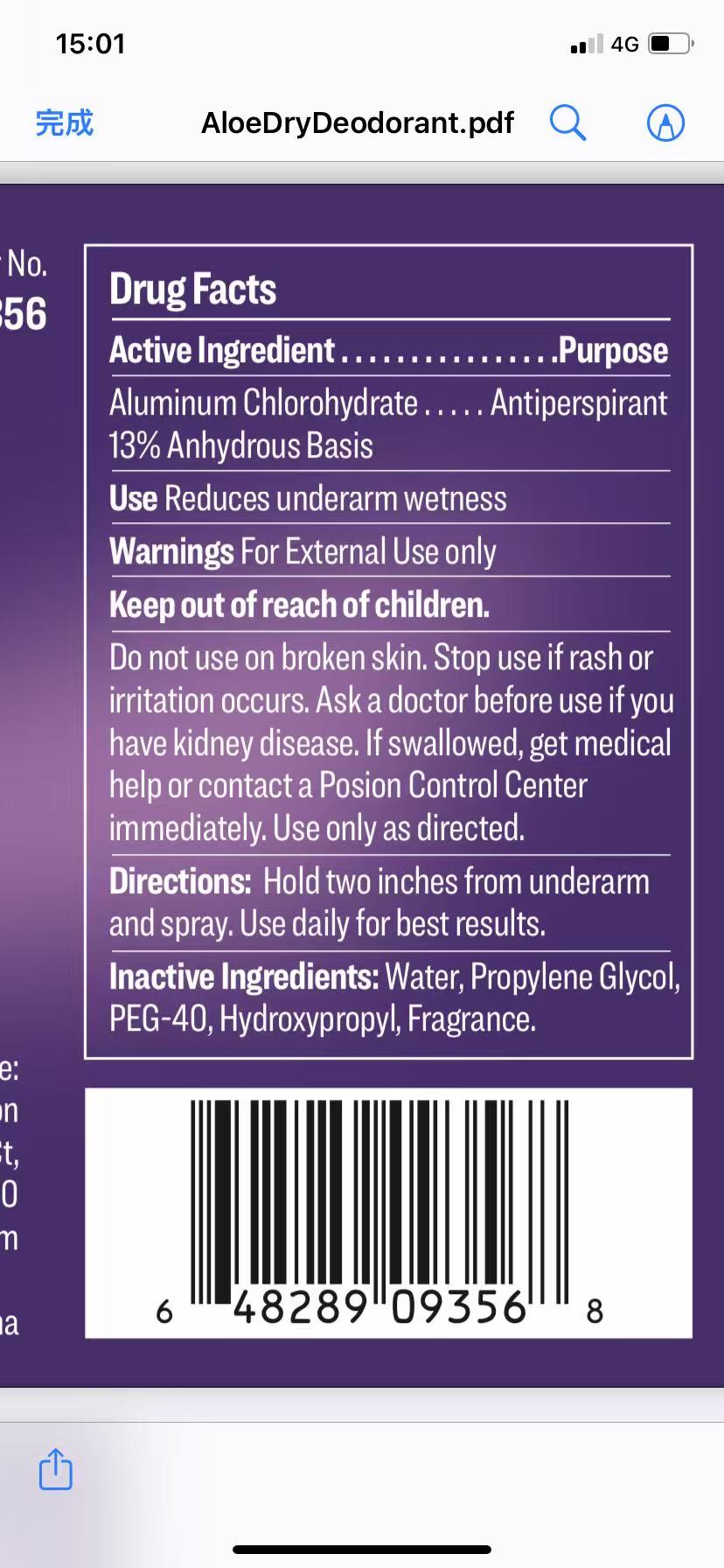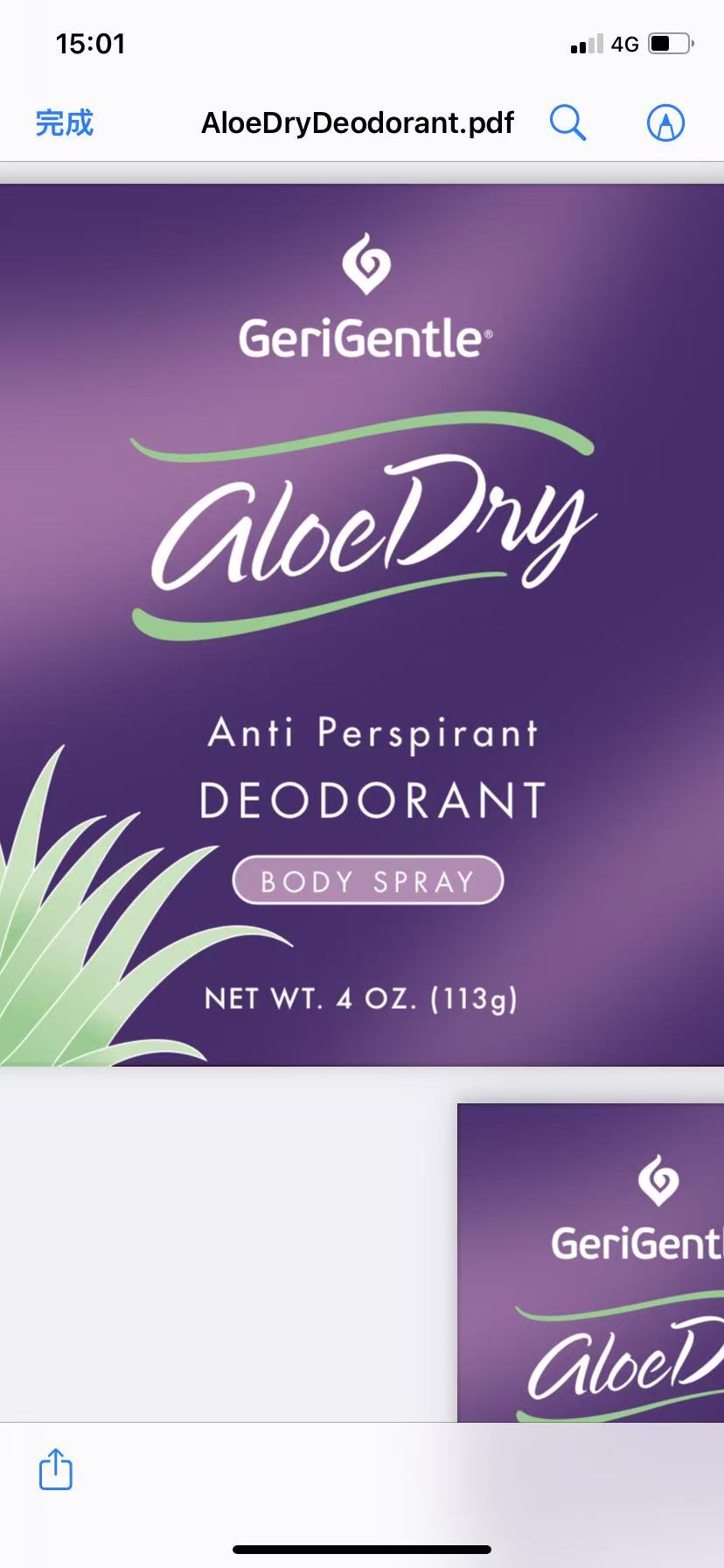 DRUG LABEL: GeriGentle Aloe Dry Anti Perspirant Deodorant Body
NDC: 85420-001 | Form: SPRAY
Manufacturer: Liufangjing Biotechnology (Yangzhou) Co., Ltd
Category: otc | Type: HUMAN OTC DRUG LABEL
Date: 20250520

ACTIVE INGREDIENTS: ALUMINUM CHLOROHYDRATE 0.13 g/1 g
INACTIVE INGREDIENTS: PROPYLENE GLYCOL; PEG-40 DISTEARATE; WATER; HYDROXYPROPYL ACRYLATE

85420-001

Active Ingredient

Aluminum Chlorohydrate: 13%

Purpose: Anti perspirant

INDICATIONS AND USAGE

Uses Reduces underarm wetness

Warnings

For external use only

Do not use on broken skin. Ask a doctor before useif you have kidney disease

Stop use if rash or irritation occurs

Keep out of reach of children.If swallowed, get medical help or contact a Poison Control Center immediately. Use only as directed.

Directions

Hold two inches from underarm and spray. Use daily for best results.

Inactive Ingredient

Water, Propylene Glycol, PEG-40, Hydroxypropyl, Fragrance